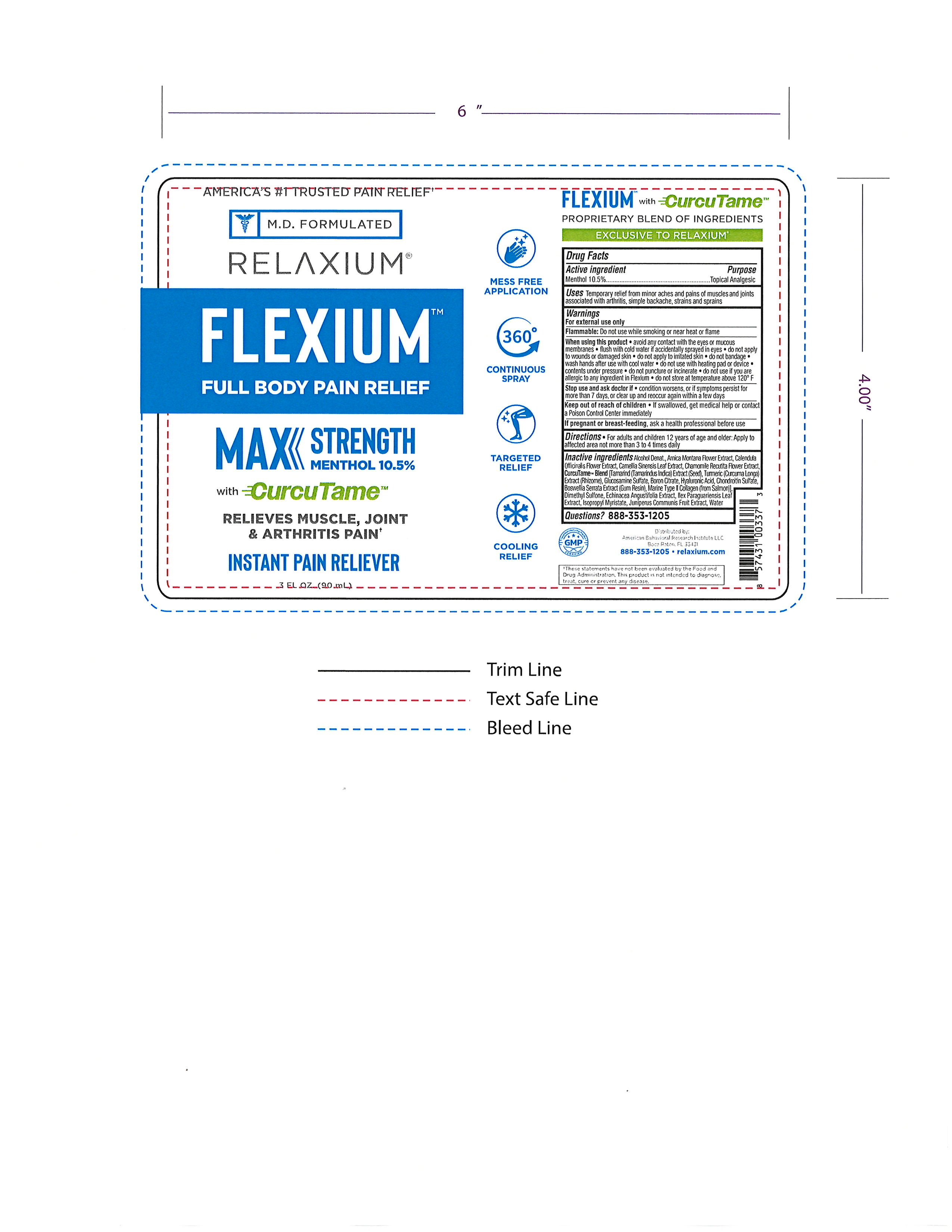 DRUG LABEL: Relaxium
NDC: 72667-080 | Form: SPRAY
Manufacturer: Inspec Solutions LLC.
Category: otc | Type: HUMAN OTC DRUG LABEL
Date: 20240904

ACTIVE INGREDIENTS: MENTHOL 10.5 g/100 g
INACTIVE INGREDIENTS: ARNICA MONTANA FLOWER; INDIAN FRANKINCENSE; GREEN TEA LEAF; HYALURONATE SODIUM; CARYA OVATA BARK; CITRIC ACID MONOHYDRATE; ALCOHOL; GLUCOSAMINE SULFATE; PROPYLENE GLYCOL; CHAMOMILE; JUNIPER BERRY; PHENOXYETHANOL; BORIC ACID; CALENDULA OFFICINALIS FLOWER; ELOSULFASE ALFA; ISOPROPYL MYRISTATE; ILEX PARAGUARIENSIS LEAF; WATER; DIMETHYL SULFONE; ECHINACEA ANGUSTIFOLIA; FRAGRANCE 13576

Flexium Full Body Pain Relief Max Strength Menthol 10.5% (IS0011-RL)

ACTIVE INGREDIENT

Menthol ........ 10.5%

PURPOSE

Topical Analgesic

INDICATIONS AND USAGE

Temporary relief from minor aches and pains of muscles and joints associated with arthritis, simple backache, strains and sprains.

WARNINGS

For external use only.

When using this product • avoid any contact with the eyes or mucous
membranes • flush with cold water if accidentally sprayed in eyes • do not apply
to wounds or damaged skin • do not apply to irritated skin • do not bandage •
wash hands after use with cool water • do not use with heating pad or device •
contents under pressure • do not puncture or incinerate • do not use if you are
allergic to any ingredient in Flexium • do not store at temperature above 120° F

Stop use and ask doctor if • condition worsens, or if symptoms persist for
more than 7 days, or clear up and reoccur again within a few days

Keep out of reach of children • If swallowed, get medical help or contact a Poison Control Center immediately

PREGNANCY OR BREAST FEEDING

If pregnant or breast-feeding, ask a health professional before use

DOSAGE AND ADMINISTRATION

Directions • For adults and children 12 years of age and older: Apply to affected area not more than 3 to 4 times daily

INACTIVE INGREDIENT

Inactive ingredients Alcohol Denat., Arnica Montana Flower Extract, Calendula
Officinalis Flower Extract, Camellia Sinensis Leaf Extract, Chamomile Recutita Flower Extract,
CurcuTame™ Blend [Tamarind (Tamarindus Indica) Extract (Seed), Turmeric (Curcuma Longa)
Extract (Rhizome), Glucosamine Sulfate, Boron Citrate, Hyaluronic Acid, Chondroitin Sulfate,
Boswellia Serrata Extract (Gum Resin), Marine Type II Collagen (from Salmon)],
Dimethyl Sulfone, Echinacea Angustifolia Extract, Ilex Paraguariensis Leaf
Extract, Isopropyl Myristate, Juniperus Communis Fruit Extract, Water

QUESTIONS

Question? 888-353-1205